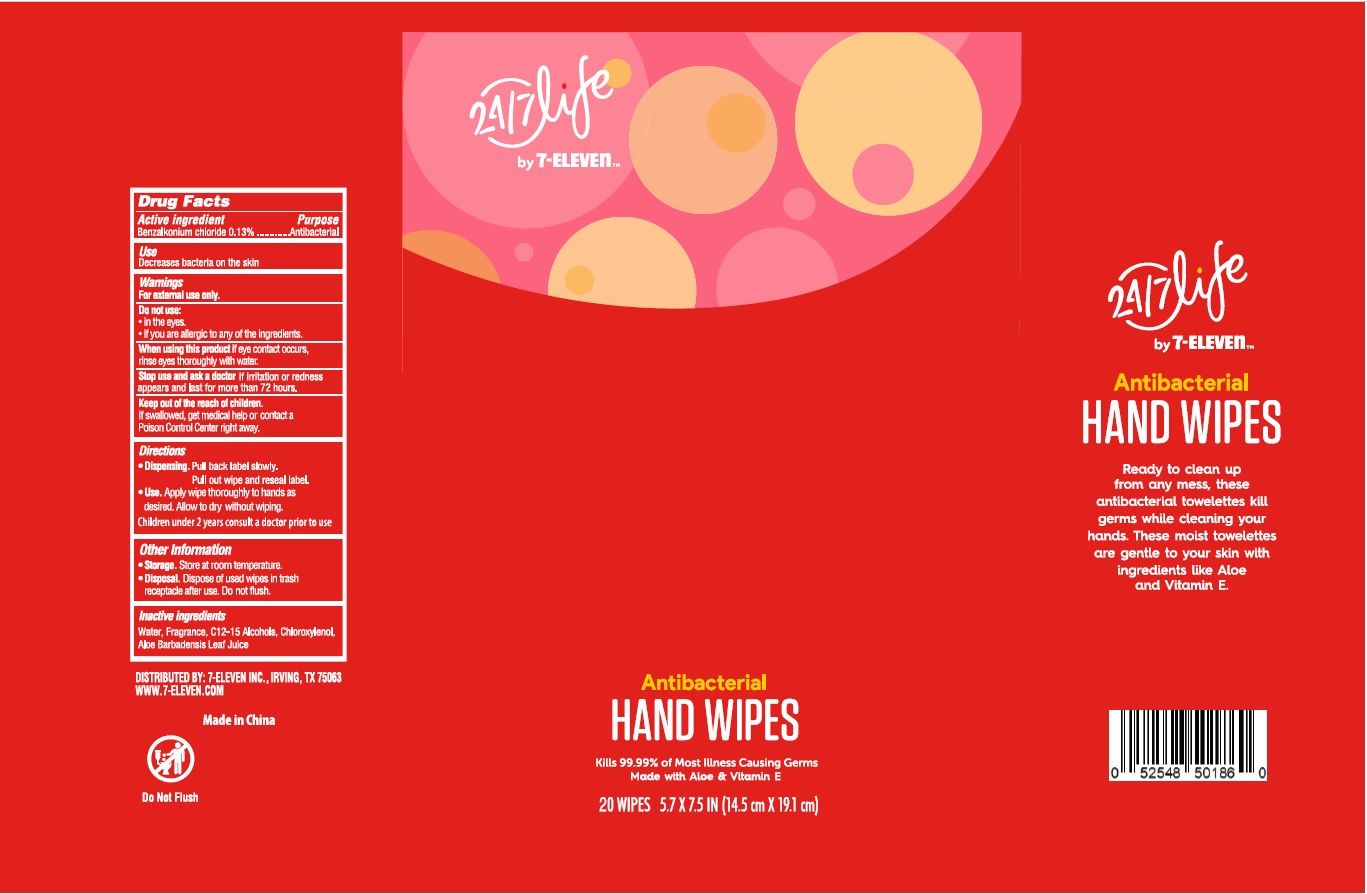 DRUG LABEL: 24 7 life by 7 Eleven
NDC: 10202-401 | Form: CLOTH
Manufacturer: 7-Eleven
Category: otc | Type: HUMAN OTC DRUG LABEL
Date: 20230222

ACTIVE INGREDIENTS: BENZALKONIUM CHLORIDE 0.13 g/100 mL
INACTIVE INGREDIENTS: C12-15 ALCOHOLS; WATER; ALOE VERA LEAF; CHLOROXYLENOL

24/7 life by 7-Eleven

Active ingredient

Benzalkonium chloride 0.13%

Purpose

Antibacterial

Use

Decreases bacteria on the skin

Warnings

For external use only.

Do not use:

- in the eyes.
- if you are allergic to any of the ingredients

When using this product

if eye contact occurs, rinse eyes thoroughly with water.

Stop use and ask a doctor

if irritation or redness appears and last for more than 72 hours.

Keep out of reach of children

If swallowed, get medical help or contact a Poison Control Center right away.

Directions

Dispensing. Pull back label slowly. Pull out wipe and reseal label.

Use. Apply wipe thoroughly to hands as desired. Allow to dry without wiping.

Children under 2 years consult a doctor prior to use

Other information

Storage: Store at room temperature.

Disposal. Dispose of used wipes in trash receptacle after use. Do not flush.

Inactive ingredients

Water, Fragrance, C12-15 Alcohols, Chloroxylenol, Aloe Barbadensis Leaf Juice